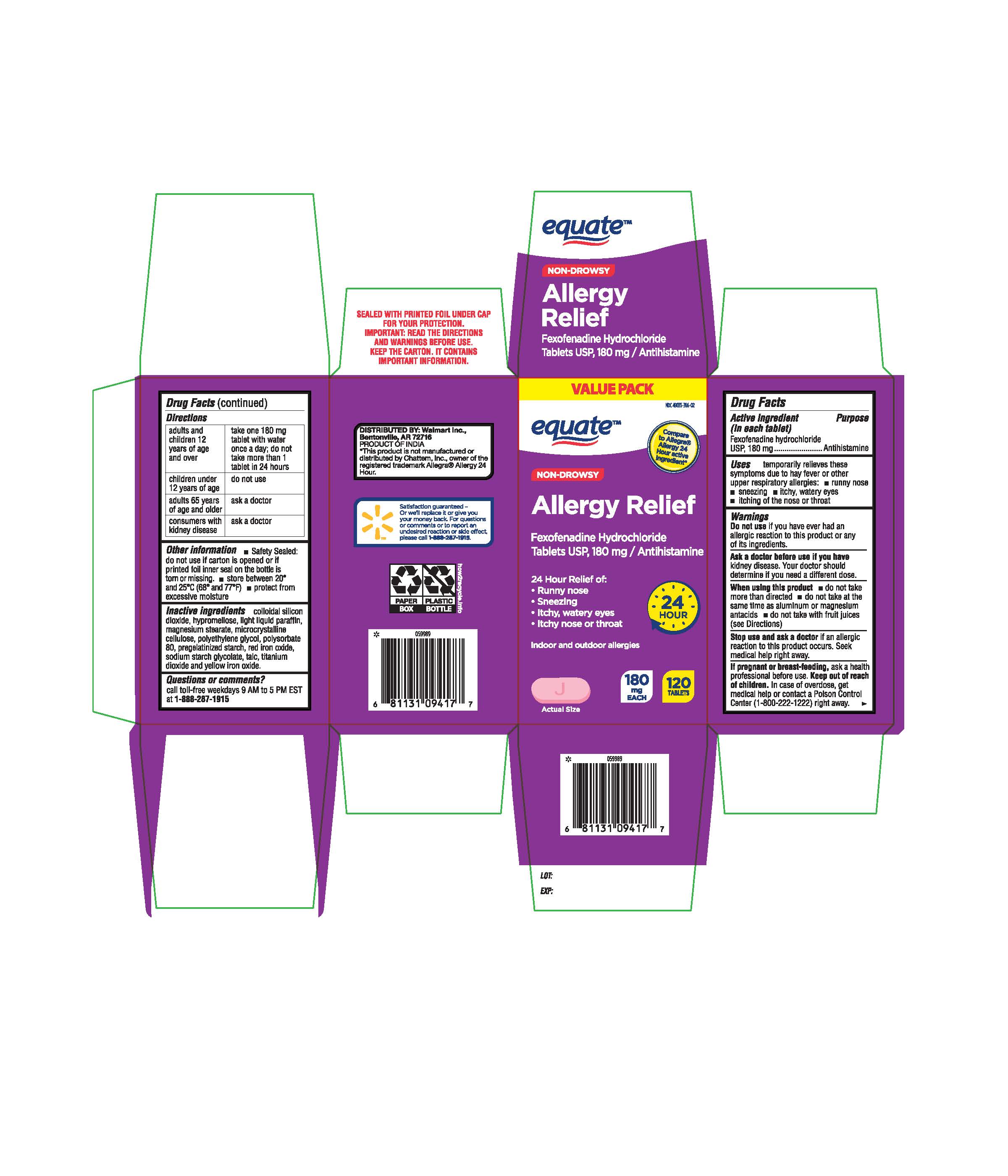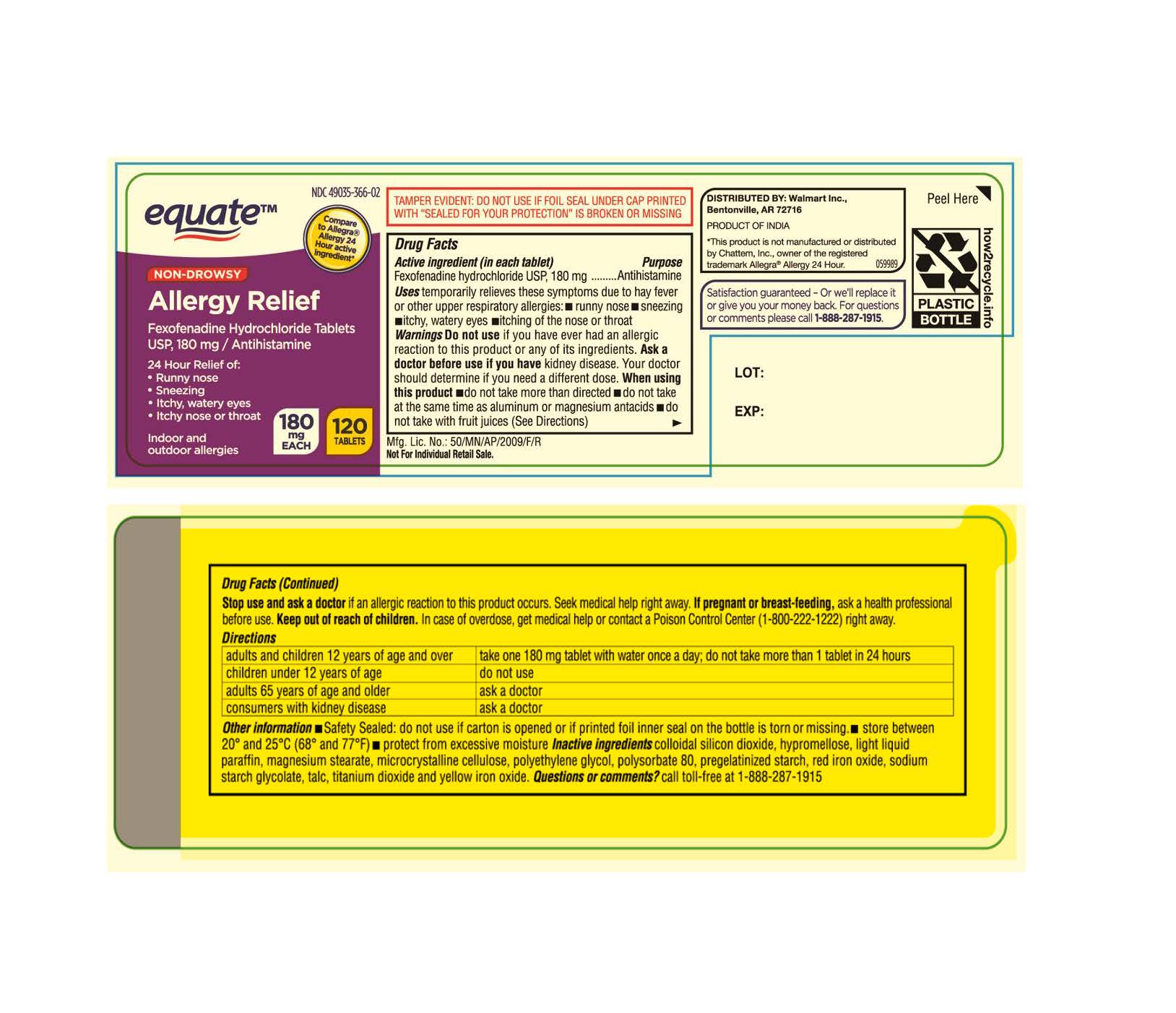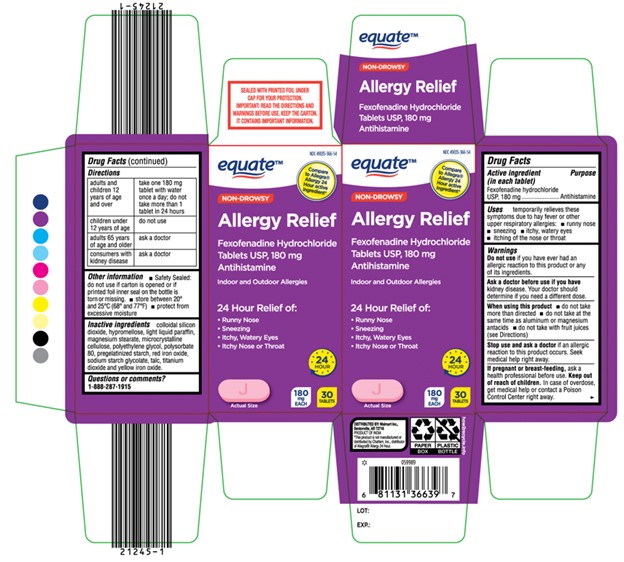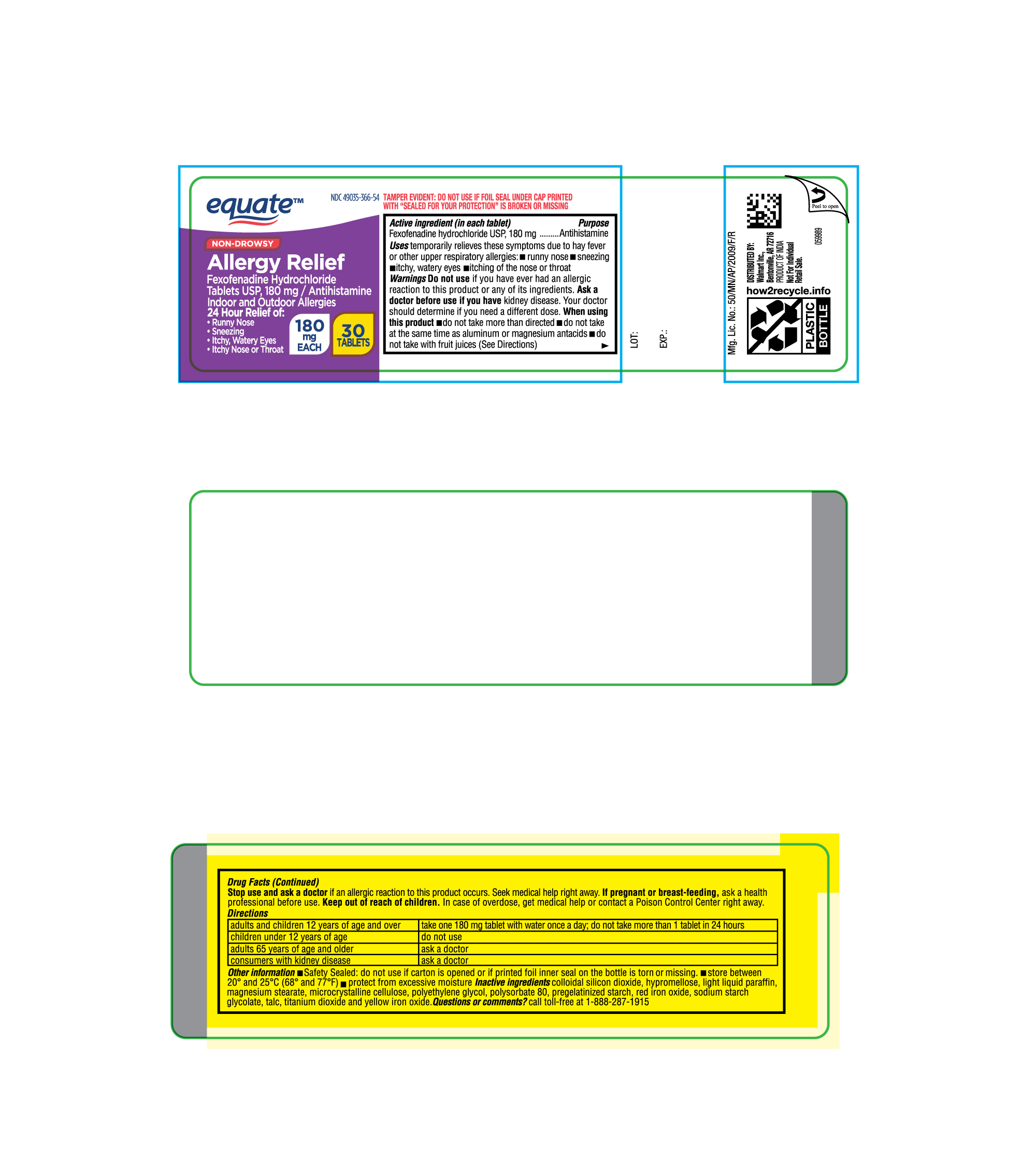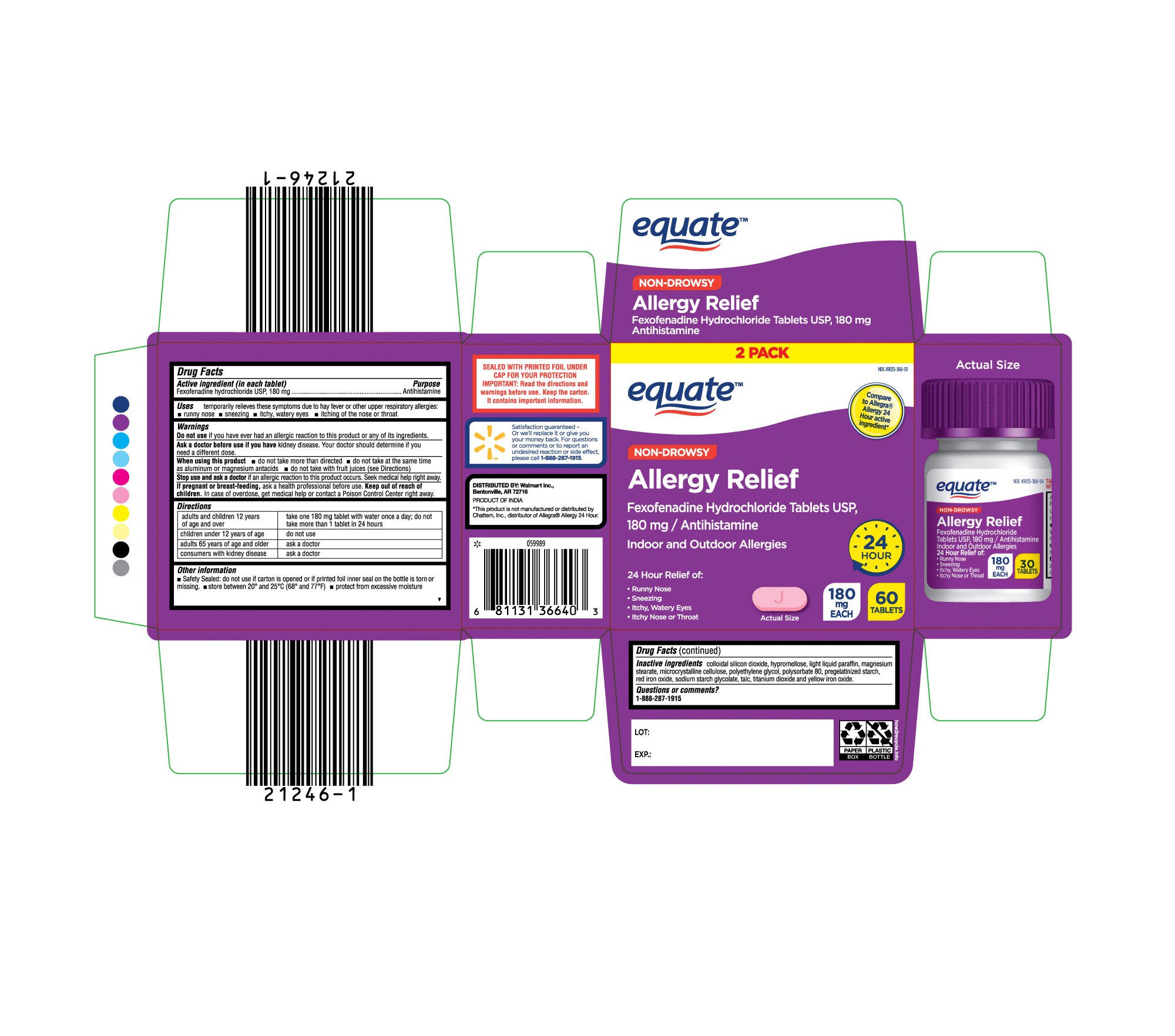 DRUG LABEL: equate allergy relief
NDC: 49035-366 | Form: TABLET
Manufacturer: Walmart Inc.
Category: otc | Type: HUMAN OTC DRUG LABEL
Date: 20250206

ACTIVE INGREDIENTS: FEXOFENADINE HYDROCHLORIDE 180 mg/1 1
INACTIVE INGREDIENTS: SILICON DIOXIDE; HYPROMELLOSE 2910 (6 MPA.S); LIGHT MINERAL OIL; MAGNESIUM STEARATE; MICROCRYSTALLINE CELLULOSE; POLYSORBATE 80; STARCH, CORN; FERRIC OXIDE RED; FERRIC OXIDE YELLOW; SODIUM STARCH GLYCOLATE TYPE A POTATO; TALC; TITANIUM DIOXIDE; POLYETHYLENE GLYCOL 6000

Fexofenadine Hydrochloride Tablets USP, 180 mg

Active ingredient(s)

Fexofenadine hydrochloride USP, 180 mg

Purpose

Antihistamine

Use(s)

temporarily relieves these symptoms due to hay fever or other upper respiratory allergies:

- runny nose
- sneezing
- itchy, watery eyes
- itching of the nose or throat

Warnings

Do not use

if you have ever had an allergic reaction to this product or any of its ingredients.

Ask a doctor or pharmacist before use if

you have kidney disease. Your doctor should determine if you need a different dose.

When using this product

- do not take more than directed
- do not take at the same time as aluminum or magnesium antacids
- do not take with fruit juices (see Directions)

Stop use and ask a doctor if

an allergic reaction to this product occurs. Seek medical help right away.

If pregnant or breast-feeding,

ask a health professional before use.

Keep out of reach of children

In case of overdose, get medical help or contact a Poison Control Center right away

Directions

adults and children 12 years of age and over | take one 180 mg tablet with water once a day; do not take more than 1 tablet in 24 hours
children under 12 years of age | do not use
adults 65 years of age and older | ask a doctor
consumers with kidney disease | ask a doctor

Other information

- Safety Sealed: do not use if carton is opened or if printed foil inner seal on the bottle is torn or missing.
- store between 20° and 25°C (68° and 77°F)
- protect from excessive moisture

Inactive ingredients

Colloidal silicon dioxide, hypromellose, light liquid paraffin, magnesium stearate, microcrystalline cellulose, polyethylene glycol, polysorbate 80, pregelatinized starch, red iron oxide, sodium starch glycolate, talc, titanium dioxide and yellow iron oxide.

Questions

call toll-free weekdays 9 AM to 5 PM EST at 1-888-588-1418

Principal Display Panel

Fexofenadine Hydrochloride Tablets, USP 180 mg 30 ct Container Label

Fexofenadine Hydrochloride Tablets, USP 180 mg 30ct Carton Label

Fexofenadine Hydrochloride Tablets, USP 180 mg 2x30 ct Carton Label

Fexofenadine Hydrochloride Tablets, USP 180 mg 120 ct Container Label

Fexofenadine Hydrochloride Tablets, USP 180 mg 120 ct Carton Label